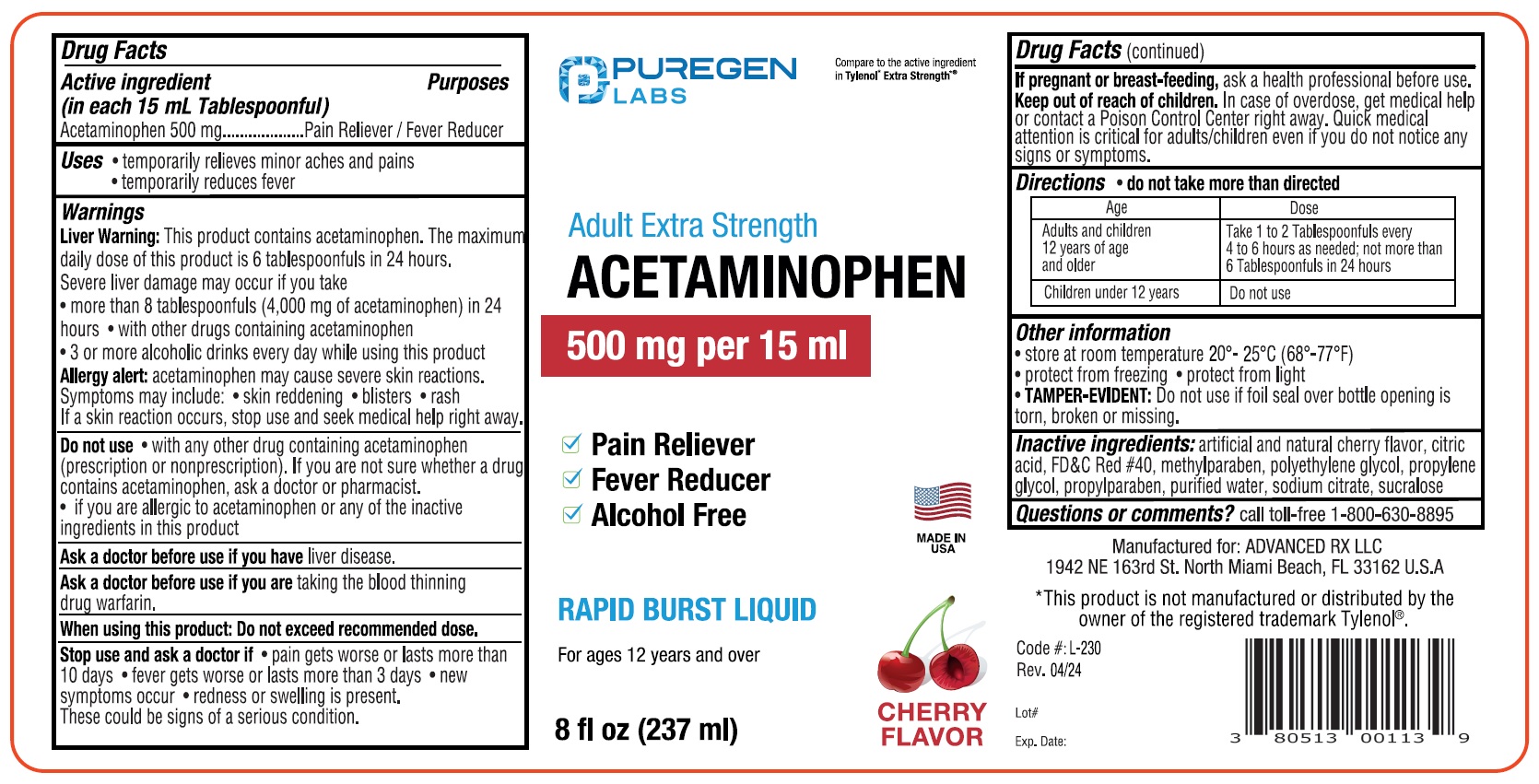 DRUG LABEL: PurgenLabs Acetaminophen
NDC: 80513-230 | Form: LIQUID
Manufacturer: Advanced Rx LLC
Category: otc | Type: HUMAN OTC DRUG LABEL
Date: 20240628

ACTIVE INGREDIENTS: ACETAMINOPHEN 500 mg/15 mL
INACTIVE INGREDIENTS: ANHYDROUS CITRIC ACID; FD&C RED NO. 40; METHYLPARABEN; POLYETHYLENE GLYCOL, UNSPECIFIED; PROPYLENE GLYCOL; PROPYLPARABEN; WATER; SODIUM CITRATE; SUCRALOSE

Active Ingredient

in each 15 mL Tablespoonful

Acetaminophen 500 mg

Purpose

Pain Reliever/Fever Reducer

Uses

- temporarily relieves minor aches and pains
- temporarily reduces fever

Warnings

Liver Warning:This product contains acetaminophen. The maximurr
daily dose of fhis product is 6 tablespoonfuls in 24 hours.
Severe liver damage may occur if you take
• more than 8 tablespoonfuls (4,000 mg of acetaminophen) in 24
hours • with other drugs containing acetaminophen
• 3 or more alcoholic drinks every day while using this product

Allergy alert acetaminophen may cause severe skin reactions.
Symptoms may include: • skin reddening • blisters • rash
If a skin reaction occurs, stop use and seek medical help right away.

Do not use • with any other drug containing acetaminophen
(prescription or nonprescription). If you are not sure whether a drug
contains acetaminophen, ask a octor or pharmacist.
• if you are allergic to acetaminophen or any of the inactive
ingredients in this product

Ask a doctor before use ff rou have liver disease.
Ask a doctor before use ff you are taking the blood thinning
drug wartarin.
When using this product Do not exceed recommended dose.

Stop use and ask a doctor If • pain gets worse or lasts more than
10 days • fever gets worse or lasts more than 3 days • new
symptoms occur • redness or swelling is present.
These could be signs of a serious condition.

PREGNANCY OR BREAST FEEDING

If pregnant or breast-feeding, ask a health professional before use.

Keep out of reach of children.

DOSAGE AND ADMINISTRATION

Age | Dose
adults and children 12 years of age and older | Take 1 to 2 Tablespoonfuls every 4 to 6 hours as needed; not more than 6 tablespoonsfuls in 24 hours
children under 12 years | Do not use

INACTIVE INGREDIENT

Inactive ingredients: artificial and natural cherry flavor, citric acid, FD&C Red #40, methylparaben, polyethylene glycol, propylene glycol, propylparaben, purified water, sodium citrate, sucralose

Questions or comments? call toll free 1-800-630-8895